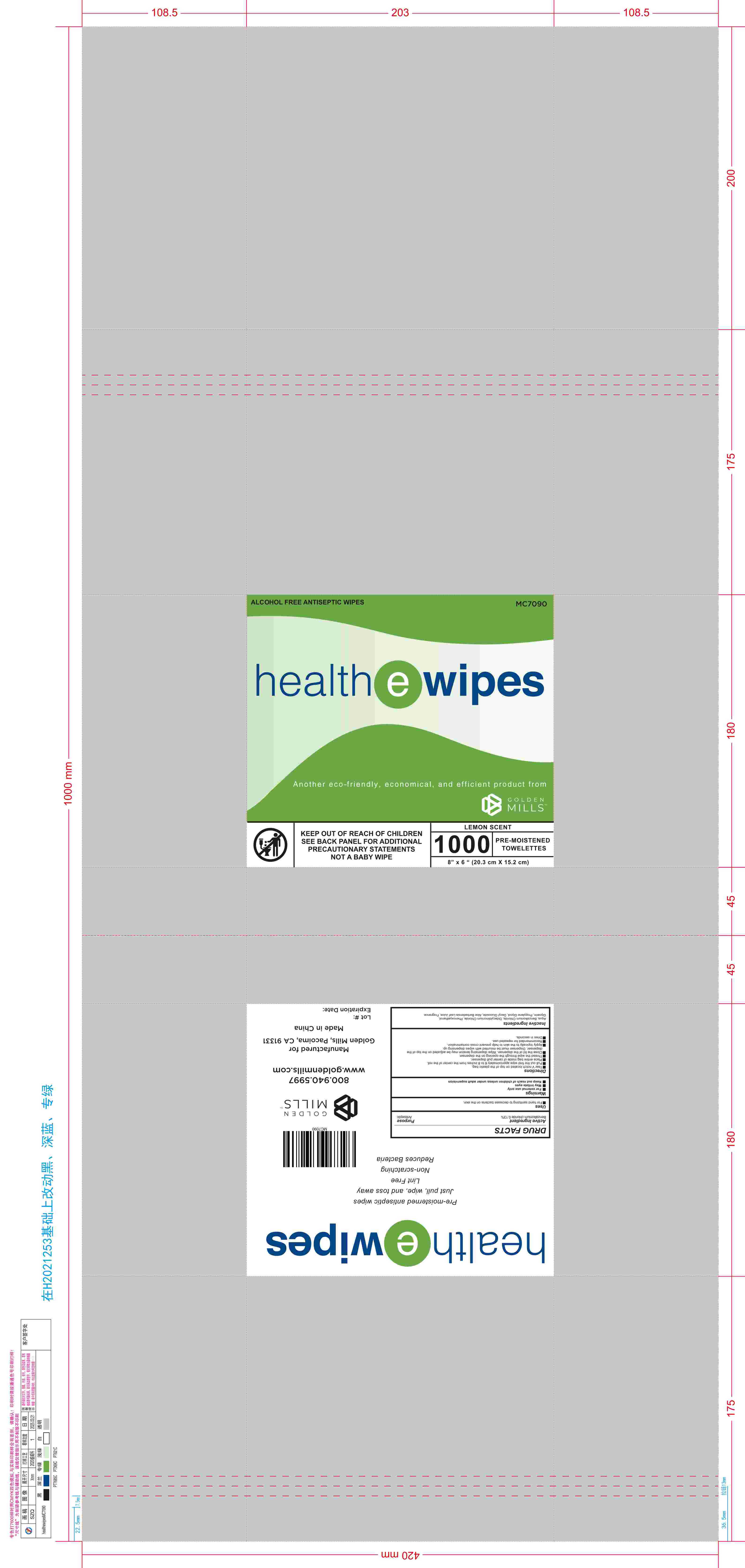 DRUG LABEL: Healthe Wipes
NDC: 84323-007 | Form: PATCH
Manufacturer: Zhejiang StarryApex Biotechnology Co., Ltd.
Category: otc | Type: HUMAN OTC DRUG LABEL
Date: 20250518

ACTIVE INGREDIENTS: BENZALKONIUM CHLORIDE 1.3 mg/1 g
INACTIVE INGREDIENTS: ALOE BARBADENSIS LEAF JUICE; AQUA; GLYCERIN; PHENOXYETHANOL; FRAGRANCE LEMON ORC2001060; DIDECYLDIMONIUM CHLORIDE; PROPYLENE GLYCOL; DECYL GLUCOSIDE

84323-007-01 healthewipesMC

ACTIVE INGREDIENT

Benzalkonium chloride 0.13%

PURPOSE

Antiseptic

WHEN USING

For hand sanitizing to decrease bacteria on the skin.

WARNINGS

For external use only
May irritate eyes

KEEP OUT OF REACH OF CHILDREN

unless under adult supervision

INDICATIONS AND USAGE

Tear V notch located on top of the plastic bag.
Pull out the first wipe approximately 6 to 8 inches from the center of the roll.
Place entire bag inside of center pull dispenser.
Thread the wipe through the opening on the dispenser.
Close the lid of the dispenser. Wipe dispensing tension may be adjusted on the top of the dispenser. Dispenser must be mounted with wipes dispensing up.
Apply topically to the skin to help prevent cross contamination.
Recommended for repeated use.
Dries in seconds.

Inactive Ingredients
Aqua, Benzalkonium Chloride, Didecyldimonium Chloride, PhenoxyethanolGlycerin, Propylene Glycol, Decyl Glucoside, Aloe Barbadensis Leaf Juice, Fragrance.

DOSAGE AND ADMINISTRATION

Pull out the first wipe approximately 6 to 8 inches from the center of the roll.